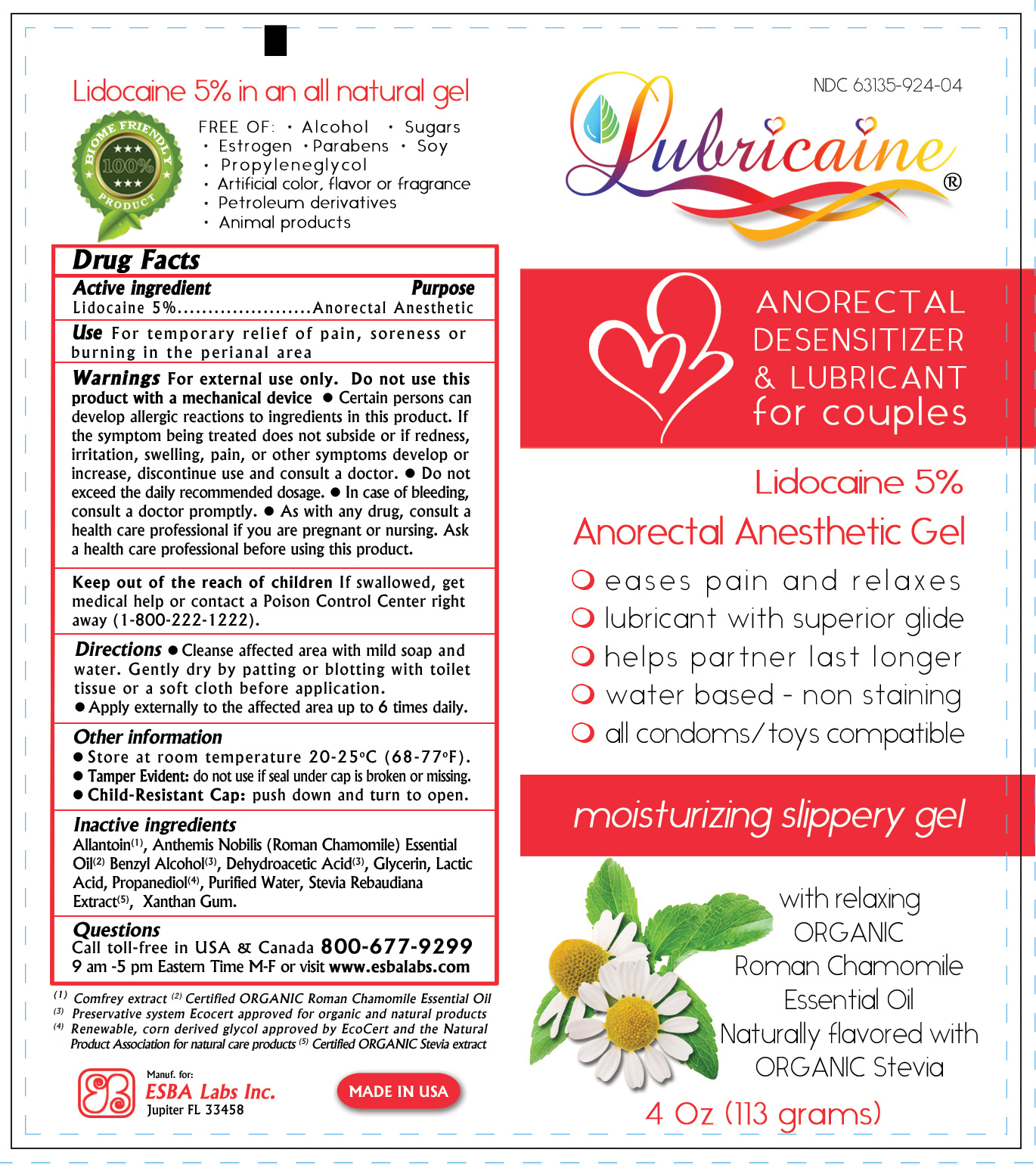 DRUG LABEL: LUBRICAINE 5
NDC: 63135-924 | Form: GEL
Manufacturer: ESBA LABORATORIES INC.
Category: otc | Type: HUMAN OTC DRUG LABEL
Date: 20260128

ACTIVE INGREDIENTS: LIDOCAINE 5 g/100 g
INACTIVE INGREDIENTS: BENZYL ALCOHOL 0.72 g/100 g; CHAMOMILE FLOWER OIL 0.1 g/100 g; LACTIC ACID, DL- 2.5 g/100 g; ALLANTOIN 0.3 g/100 g; STEVIA REBAUDIUNA LEAF 1 g/100 g; GLYCERIN 25 g/100 g; PROPANEDIOL 38.3 g/100 g; XANTHAN GUM 2 g/100 g; DEHYDROACETIC ACID 0.08 g/100 g

LUBRICAINE 5

Active Ingredient

Lidocaine 5%

Purpose

Anorectal Anesthetic

Warnings

For external use only.

Uses

For temporary relief of pain, soreness or burning in the perianal area

When using this product

Do not use this product with a mechanical device. Certain persons can develop allergic reactions to ingredients in this product.

Stop use and ask a doctor if

- Certain persons can develop allergic reactions to ingredients in this product.
- If the symptom being treated does not subside or if redness, irritation, swelling, pain, or other symptoms develop or increase, discontinue use and consult a doctor.
- Do not exceed the daily recommended dosage.
- In case of bleeding, consult a doctor promptly.
- As with any drug, consult a health care professional if you are pregnant or nursing. Ask a health care professional before using this product.

Keep out of the reach of children

If swallowed, get medical help or contact a Poison Control Center right away (1-800-222-1222).

Directions

- Cleanse affected area with mild soap and water. Gently dry by patting or blotting with toilet tissue or a soft cloth before application.
- Apply externally to the affected area up to 6 times daily.

Other Information

- Store at room temperature 20-25oC (68-77oF).
- Tamper Evident: do not use if seal under cap is broken or missing.
- Child-Resistant Cap: push down and turn to open.

Inactive Ingredients

Allantoin, Anthemis Nobilis (Roman Chamomile) Essential Oil, Benzyl Alcohol, Dehydroacetic Acid, Glycerin, Lactic Acid, Propanediol, Purified Water, Stevia Rebaudiana Extract, Xanthan Gum.

Questions

Call toll-free in USA & Canada 800-677-9299 9 am -5 pm Eastern Time M-F or visit www.esbalabs.com.